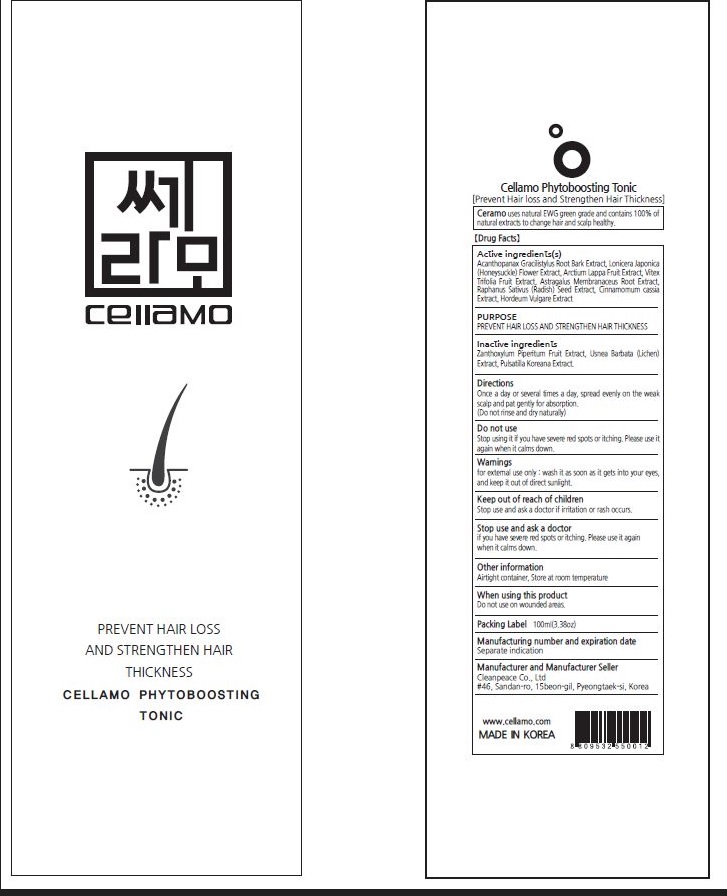 DRUG LABEL: Cellamo phytoboosting Tonic
NDC: 77818-305 | Form: SPRAY
Manufacturer: Cleanpeace Co., Ltd
Category: otc | Type: HUMAN OTC DRUG LABEL
Date: 20221216

ACTIVE INGREDIENTS: ELEUTHEROCOCCUS NODIFLORUS ROOT BARK 12.375 g/100 mL; HORDEUM VULGARE WHOLE 12.375 g/100 mL; LONICERA JAPONICA FLOWER 12.375 g/100 mL; VITEX TRIFOLIA FRUIT 12.375 g/100 mL; ASTRAGALUS PROPINQUUS ROOT 12.375 g/100 mL; RAPHANUS SATIVUS VAR. SATIVUS SEED 12.375 g/100 mL; CHINESE CINNAMON 12.375 g/100 mL; ARCTIUM LAPPA FRUIT 12.375 g/100 mL
INACTIVE INGREDIENTS: PULSATILLA KOREANA ROOT; USNEA BARBATA; ZANTHOXYLUM PIPERITUM FRUIT PULP

Active ingredients

Acanthopanax Gracilistylus Root Bark Extract, Lonicera Japonica (Honeysuckle) Flower Extract, Arctium Lappa Fruit Extract, Vitex Trifolia Fruit Extract, Astragalus Membranaceus Root Extract, Raphanus Sativus (Radish) Seed Extract, Cinnamomum cassia Extract, Hordeum Vulgare Extract

PURPOSE

PREVENT HAIR LOSS AND STRENGTHEN HAIR THICKNESS

Inactive ingredients

Zanthoxylum Piperitum Fruit Extract, Usnea Barbata (Lichen) Extract, Pulsatilla Koreana Extract.

Directions

Once a day or several times a day, spread evenly on the weak scalp and pat gently for absorption. (Do not rinse and dry naturally)

Do not use

Stop using it if you hane severe red spots or itching. Please use it again when it calms down .

Warnings

for external use only : wash it as soon as it gets into your eyes, and keep it out of direct sunlight.

Keep out of reach of children. Stop use and ask a doctor if irritation or rash occurs.

Stop use and ask a doctor

if you hane severe red spots or itching. Please use it again when it calms down.

When using this product

Do not use on wounded areas. Be careful not to wash with water after use as it may cause hair loss or discoloration

Other information

Airtight container, Store at room temperature

Label

77818-302-02